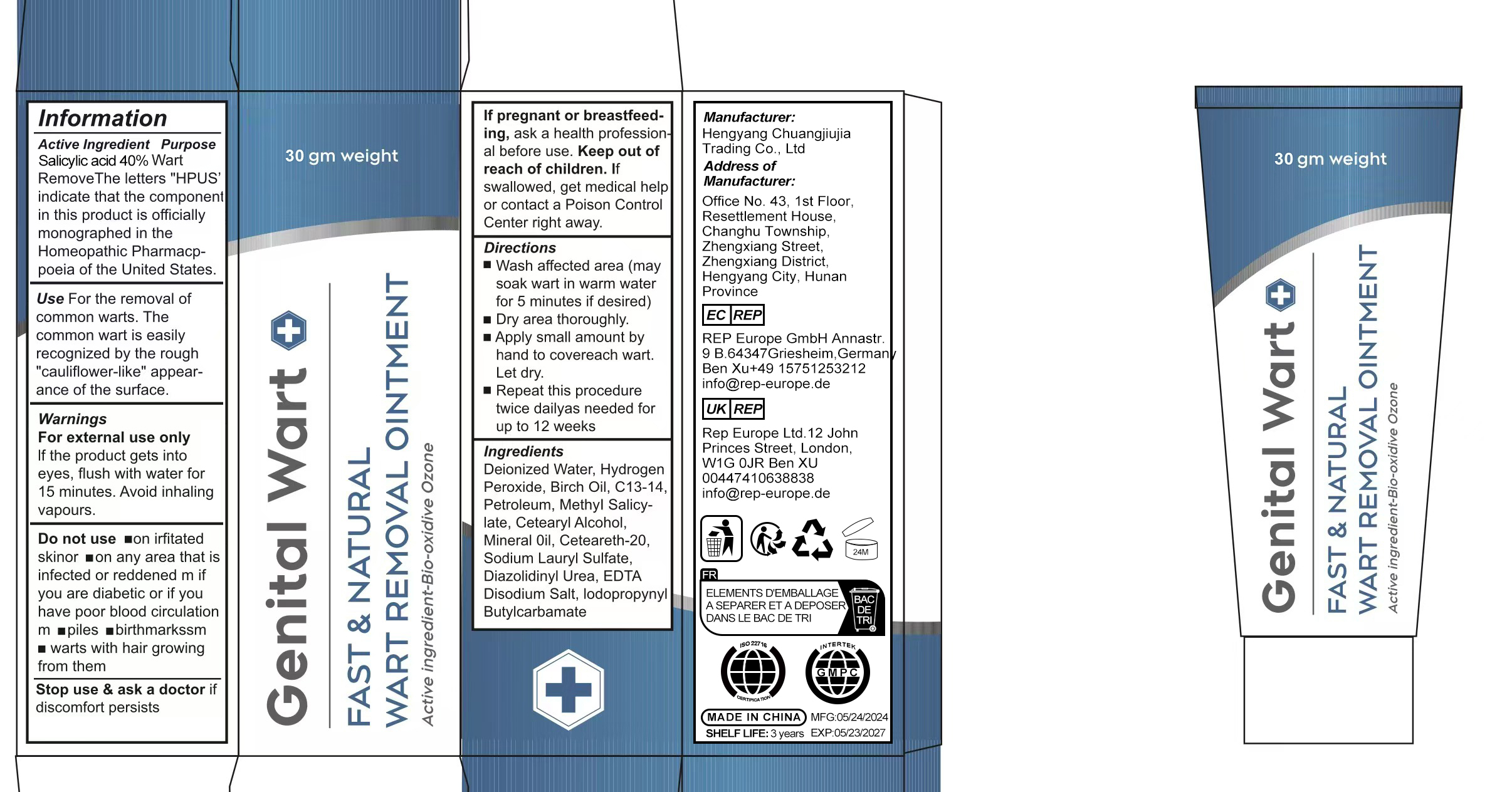 DRUG LABEL: Genital wart removal onitment
NDC: 84735-001 | Form: OINTMENT
Manufacturer: Hengyang Chuangjiujia Trading Co., Ltd.
Category: otc | Type: HUMAN OTC DRUG LABEL
Date: 20240913

ACTIVE INGREDIENTS: SALICYLIC ACID 0.4 g/1 g
INACTIVE INGREDIENTS: HYDROGEN PEROXIDE; BETULA PENDULA TAR OIL; MINERAL OIL; WATER; C13-14 ISOPARAFFIN; IODOPROPYNYL BUTYLCARBAMATE; METHYL SALICYLATE; LIQUID PETROLEUM; DIAZOLIDINYL UREA; EDETATE DISODIUM; CETOSTEARYL ALCOHOL; POLYOXYL 20 CETOSTEARYL ETHER; SODIUM LAURYL SULFATE

Genital wart removal onitment

Genital wart removal onitment

ACTIVE INGREDIENT

Salicylic acid 40%

PURPOSE

WART REMOVAL

INDICATIONS AND USAGE

Use For the removal ofcommon warts. Thecommon wart is easilyrecognized by the rough"cauliflower-like" appear-ance of the surface.

WARNINGS

For external use onlyIf the product gets intoeyes, flush with water for15 minutes. Avoid inhalingvapours

Do not use on irfitatedskinor on any area that isinfected or reddened m ifyou are diabetic or if youhave poor blood circulationm piles birthmarkssm warts with hair growingfrom them

WHEN USING

If pregnant or breastfeed-ing, ask a health profession.al before use. Keep out ofreach of children. lfswallowed, get medical helpor contact a Poison ControlCenter right away.

KEEP OUT OF REACH OF CHILDREN

Keep out ofreach of children. lfswallowed, get medical helpor contact a Poison ControlCenter right away.

Stop use & ask a doctor ifdiscomfort persists

DOSAGE AND ADMINISTRATION

Wash affected area (maysoak wart in warm waterfor 5 minutes if desired)
Dry area thoroughly.
Apply small amount byhand to covereach wart.Let dry.
Repeat this proceduretwice dailyas needed forup to 12 weeks

INACTIVE INGREDIENT

Deionized Water
Hydrogen Peroxide
Birch Oil
Petroleum
C13-14
Methyl Salicy-late
Cetearyl Alcohol
Mineral 0il
Ceteareth-20
Sodium Lauryl Sulfate
Diazolidinyl Urea
EDTA Disodium Salt
lodopropynyl Butylcarbamate